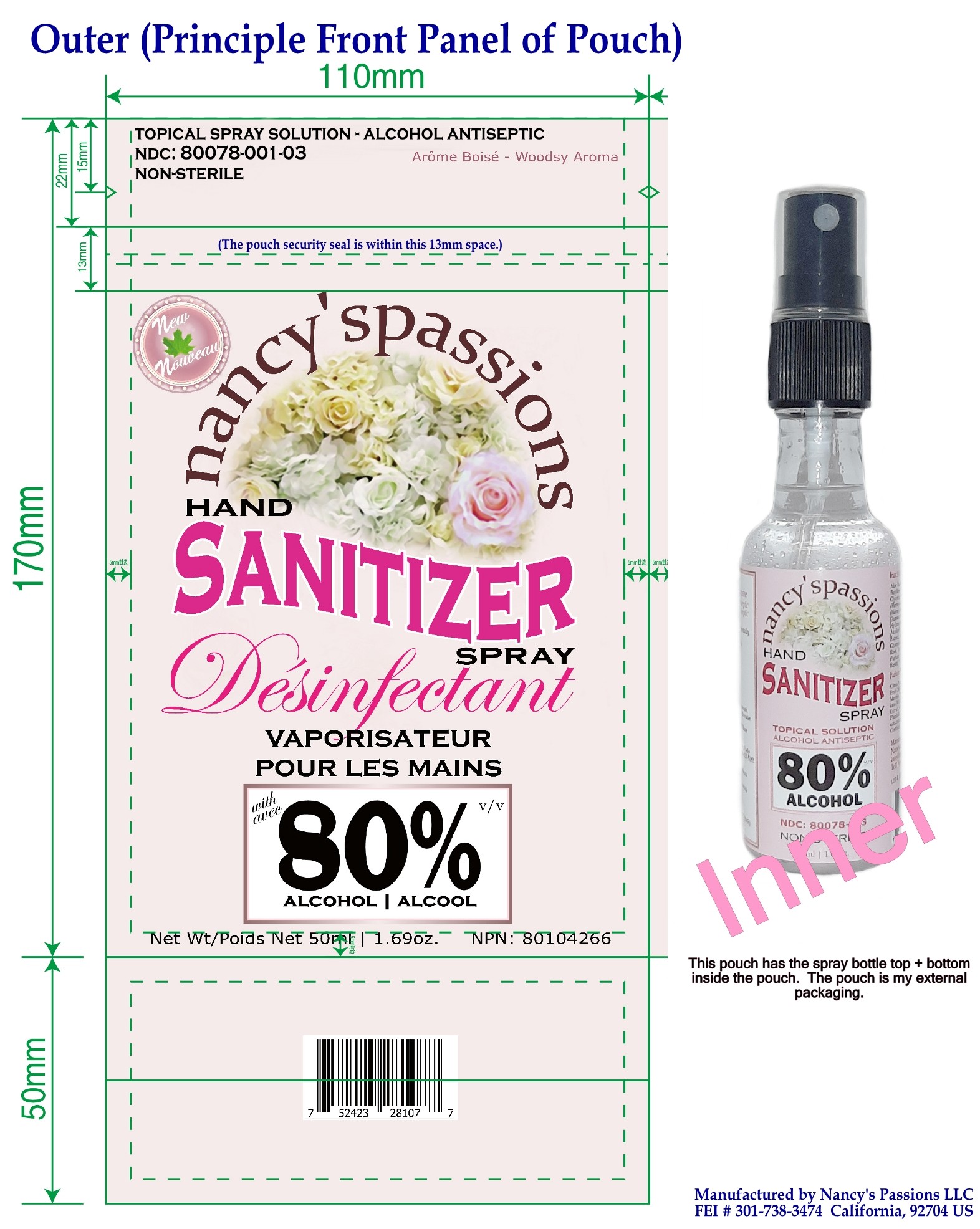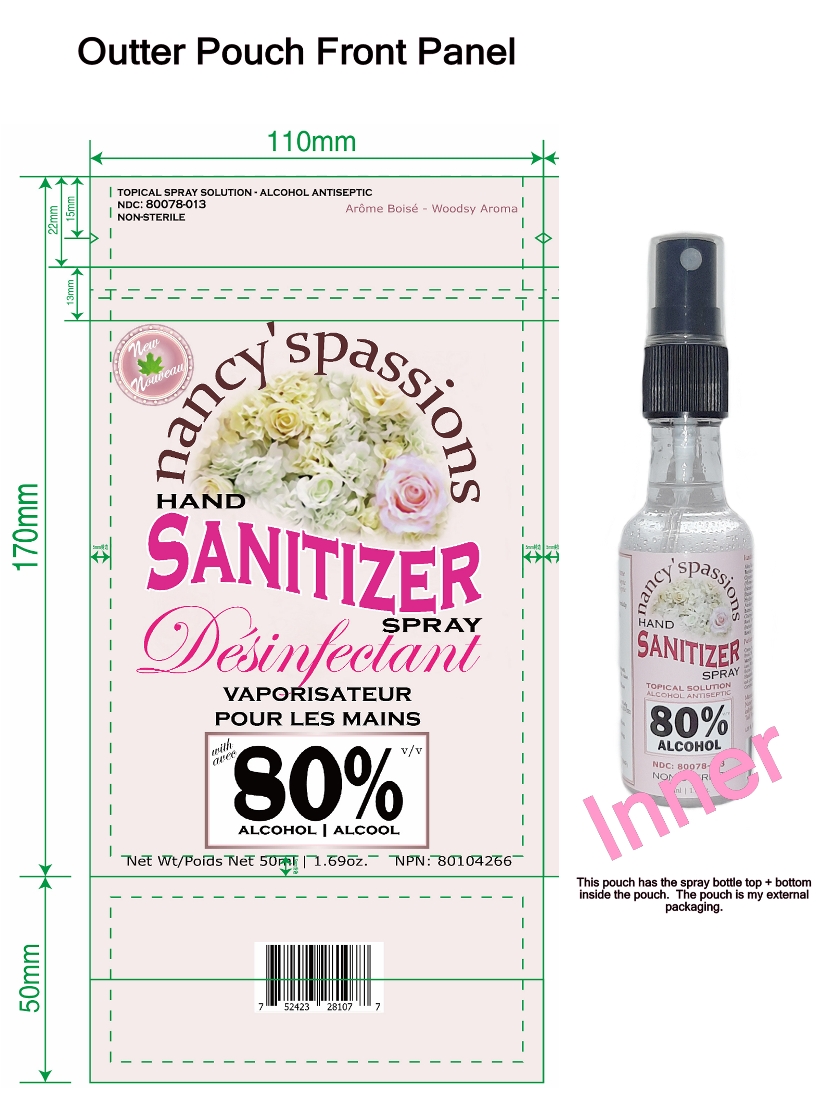 DRUG LABEL: Hand Sanitizer
NDC: 80078-001 | Form: LIQUID
Manufacturer: Nancy's Passions LLC
Category: otc | Type: HUMAN OTC DRUG LABEL
Date: 20201126

ACTIVE INGREDIENTS: ISOPROPYL ALCOHOL 0.013 mL/100 mL; ALCOHOL 80 mL/100 mL
INACTIVE INGREDIENTS: CITRUS AURANTIUM FRUIT OIL 0.005 mL/100 mL; LAVENDER OIL 0.02 mL/100 mL; SPEARMINT OIL 0.01 mL/100 mL; PROPYLENE GLYCOL 8.431 mL/100 mL; 2-AMINO-1,3-PROPANEDIOL 2.418 mL/100 mL; BENZYL ALCOHOL 0.0278 mL/100 mL; GLYCERIN 0.581 mL/100 mL; ALOE VERA LEAF 28.5158 mL/100 mL; RHODIOLA ROSEA ROOT 0.013 mL/100 mL; VACCINIUM ANGUSTIFOLIUM WHOLE 0.013 mL/100 mL; TETRASODIUM GLUTAMATE DIACETATE 0.022 mL/100 mL; BUTYLENE GLYCOL 3.2833 mL/100 mL; PHENOXYETHANOL 0.332 mL/100 mL; SAGE OIL 0.02 mL/100 mL; XANTHAN GUM 0.066 mL/100 mL; PANTHENOL 0.8165 mL/100 mL; HYALURONATE SODIUM 0.022 mL/100 mL; DECYL GLUCOSIDE 0.022 mL/100 mL; COCO GLUCOSIDE 0.017 mL/100 mL; SODIUM HYDROXYMETHYLGLYCINATE 0.004 mL/100 mL; POLYSORBATE 20 0.173 mL/100 mL; LONICERA JAPONICA FLOWER 0.0545 mL/100 mL; LONICERA CAPRIFOLIUM FLOWER 0.0545 mL/100 mL; ROSA DAMASCENA FLOWER OIL 0.035 mL/100 mL; BETAINE 0.026 mL/100 mL; WITCH HAZEL 0.01 mL/100 mL; CEDRUS ATLANTICA BARK OIL 0.1 mL/100 mL; VANILLA PLANIFOLIA OIL 0.06 mL/100 mL

80% Alcohol Hand Sanitizer Spray Topical Antiseptic Non-Sterile

This is a hand sanitizer manufactured according to the Temporary Policy for Preparation of Certain Alcohol-Based Hand Sanitizer Products During the Public Health Emergency (CoViD-19); Guidance for Industry.

The hand sanitizer is manufactured using only the following United States Pharmacopoeia (USP) grade ingredients in the preparation of the product (percentage in final product formulation) consistent with World Health Organization (WHO) recommendations:

1. Alcohol (ethanol) (USP or Food Chemical Codex (FCC) grade) (80%, volume/volume (v/v)) in an aqueous solution denatured according to Alcohol and Tobacco Tax and Trade Bureau regulations in 27 CFR part 20.
2. Glycerol (1.45% v/v).
3. Hydrogen peroxide (0.125% v/v).
4. Sterile distilled water or boiled cold water.

The firm does not add other active or inactive ingredients. Different or additional ingredients may impact the quality and potency of the product.

Active Ingredient(s)

Alcohol 80% v/v. Purpose: Antiseptic

Purpose

Antiseptic, Hand Sanitizer

Use

Hand Sanitizer to help reduce bacteria that potentially can cause disease. For use when soap and water are not available.

Warnings

For external use only. Flammable. Keep away from heat or flame

Do not use

- in children less than 2 months of age
- on open skin wounds

When using this product keep out of eyes, ears, and mouth. In case of contact with eyes, rinse eyes thoroughly with water.
Stop use and ask a doctor if irritation or rash occurs. These may be signs of a serious condition.
Keep out of reach of children. If swallowed, get medical help or contact a Poison Control Center right away.

Stop use and ask a doctor if irritation or rash occurs. These may be signs of a serious condition.

Keep out of reach of children. If swallowed, get medical help or contact a Poison Control Center right away.

Directions

- Place enough product on hands to cover all surfaces. Rub hands together until dry.
- Supervise children under 6 years of age when using this product to avoid swallowing.

Other information

- Store between 15-30C (59-86F)
- Avoid freezing and excessive heat above 40C (104F)

Inactive ingredients

glycerin, hydrogen peroxide, purified water USP

Package Label - Principal Display Panel

50 mL NDC: 80078-001-03

Topical Spray Solution
Alcohol Antiseptic
Hand Sanitizer
80% Alcohol
Non-sterile

The image shows the front panel of the pouch. It is manufactured in California by me. The rear has the drug facts and pertinent information. Inside the pouch, there is the product that also has the appropriate label and all info (front and back). I am using a pouch as a security feature.